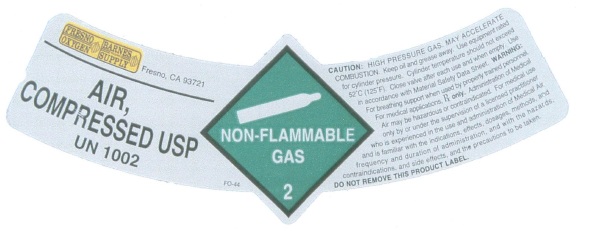 DRUG LABEL: Air
NDC: 11564-003 | Form: GAS
Manufacturer: Fresno Oxygen and Welding Suppliers
Category: prescription | Type: HUMAN PRESCRIPTION DRUG LABEL
Date: 20100219

ACTIVE INGREDIENTS: Air 1000 mL/1 L

Air

PACKAGE LABEL

FRESNO OXYGEN
BARNES WELDING SUPPLY
Fresno, CA 93721
AIR,
COMPRESSED
UN1002
FO-44
NON-FLAMMABLE GAS 2
CAUTION: HIGH PRESSURE GAS. MAY ACCELERATE COMBUSTION. Keep oil and grease away. Use equipment rated for cylinder pressure. Cylinder temperature should not exceed 52 degrees C (125 degrees F). Close valve after each use and when empty. Use in accordance with the Material Safety Data Sheet. WARNING: For breathing support when used by properly trained personnel. For medical applications, Rx only. Administration of medical air may be hazardous or contraindicated. For medical use only by or under the supervision of a licensed practitioner who is experienced in the use and administration of medical air and is familiar with the indications, effects, dosages, methods, and frequency and duration of administration and with the hazards, contraindications and side effects, and the precautions to be taken.
DO NOT REMOVE THIS PRODUCT LABEL.